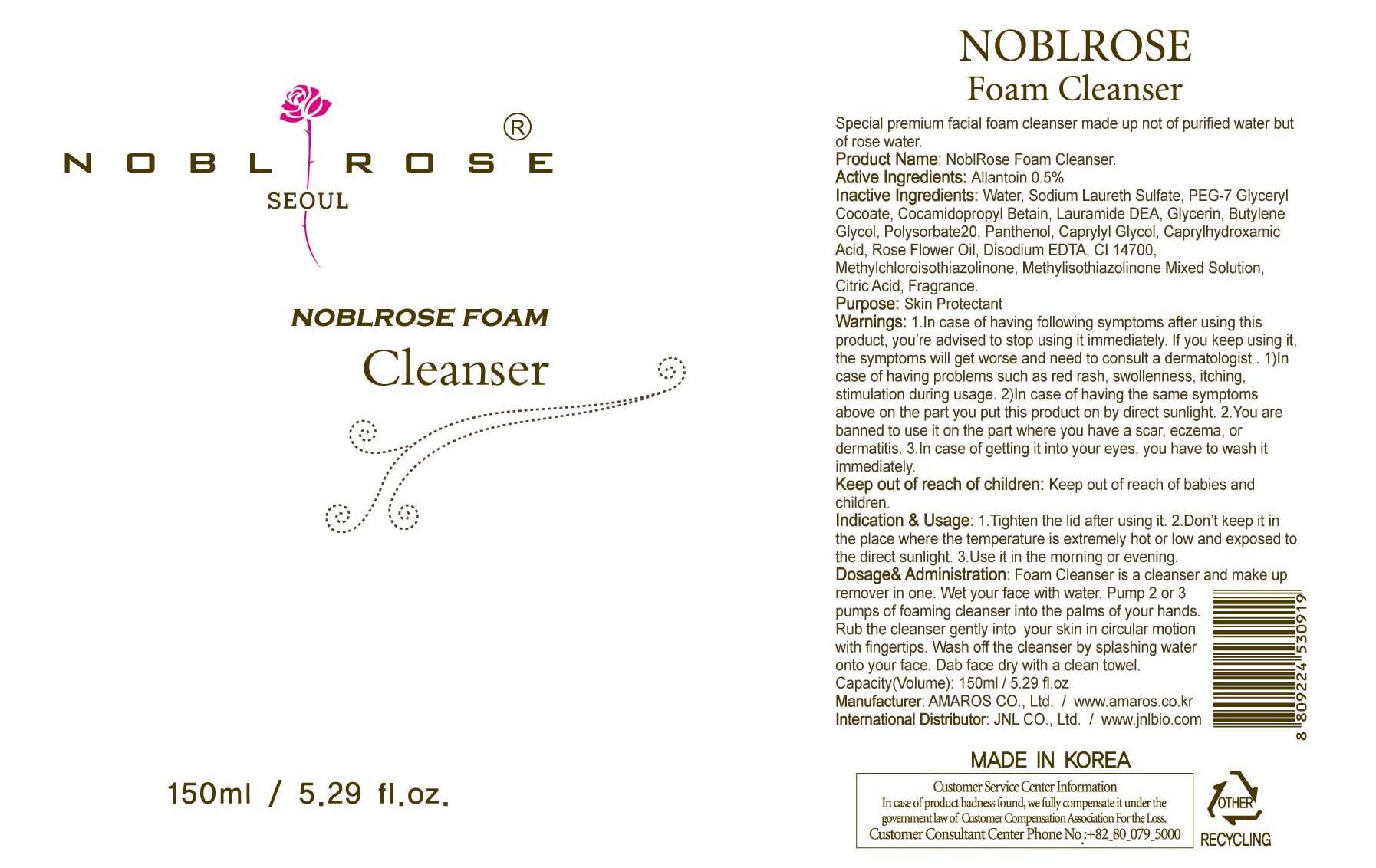 DRUG LABEL: NoblRose Foam Cleanser
NDC: 60899-070 | Form: LIQUID
Manufacturer: AMAROS CO., LTD.
Category: otc | Type: HUMAN OTC DRUG LABEL
Date: 20190411

ACTIVE INGREDIENTS: Allantoin 0.75 mg/150 mL
INACTIVE INGREDIENTS: Water; Glycerin

ACTIVE INGREDIENT

Active Ingredient: Allantoin 0.5%

INACTIVE INGREDIENT

Inactive Ingredients: Water, Sodium Laureth Sulfate, PEG-7 Glyceryl Cocoate, Cocamidopropyl Betain, Lauramide DEA, Glycerin, Butylene Glycol, Polysorbate20, Panthenol, Caprylyl Glycol, Caprylhydroxamic Acid, Rose Flower Oil, Disodium EDTA, CI 14700, Methylchloroisothiazolinone, Methylisothiazolinone Mixed Solution, Citric Acid, Fragrance.

PURPOSE

Purpose: Skin Protectant

WARNINGS

Warnings: 1. In case of having following symptoms after using this product, you're advised to stop using it immediately. If you keep using it, the symptoms will get worse and need to consult a dermatologist. 1) In case of having problems such as red rash, swollenness, itching, stimulation during usage. 2) In case of having the same symptoms above on the part you put this product on by direct sunlight. 2. You are banned to use it on the part where you have a scar, eczema, or dermatitis. 3. In case of getting it into your eyes, you have to wash it immediately.

Keep out of reach of children: Keep out of reach of babies and children.

INDICATIONS AND USAGE

Indication and Usage: 1. Tighten the lid after using it. 2. Don't keep it in the place where the temperature is extremely hot or low and exposed to the direct sunlight. 3. Use it in the morning or evening.

Dosage and Administration: Foam Cleansing is a cleanser and make up remover in one. Wet your face with water. Pump 2 or 3 pumps of foaming cleanser into the palms of your hands. Rub the cleanser gently into your skin in circular motion with fingertips. Wash off the cleanser by splashing water onto your face. Dab face dry with a clean towel.